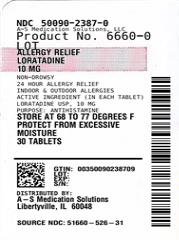 DRUG LABEL: Loratadine Allergy Relief
NDC: 50090-2387 | Form: TABLET
Manufacturer: A-S Medication Solutions
Category: otc | Type: HUMAN OTC DRUG LABEL
Date: 20260219

ACTIVE INGREDIENTS: LORATADINE 10 mg/1 1
INACTIVE INGREDIENTS: ZEA MAYS (CORN) STARCH; LACTOSE MONOHYDRATE; MAGNESIUM STEARATE

Loratadine Allergy Relief

Drug Facts

Active ingredient (in each tablet)

Loratadine, USP 10 mg

Purpose

Antihistamine

Uses

temporarily relieves these symptoms due to hay fever or other upper respiratory allergies:

- runny nose
- itchy, watery eyes
- sneezing
- itching of the nose or throat

Warnings

Do not use if you have ever had an allergic reaction to this product or any of its ingredients.

Ask a doctor before use if you have liver or kidney disease. Your doctor should determine if you need a different dose.

When using this product do not take more than directed. Taking more than directed may cause drowsiness.

Stop use and ask a doctor if an allergic reaction to this product occurs. Seek medical help right away.

PREGNANCY OR BREAST FEEDING

If pregnant or breast-feeding, ask a health professional before use.

Keep out of reach of children. In case of overdose, get medical help or contact a Poison Control Center right away (1-800-222-1222).

Directions

adults and children 6 years and over | 1 tablet daily; not more than 1 tablet in 24 hours
children under 6 years of age | ask a doctor
consumers with liver or kidney disease | ask a doctor

Other Information

- store between 20° to 25° C (68° to 77° F)
- protect from excessive moisture
- TAMPER EVIDENT: DO NOT USE IF BLISTER UNITS ARE TORN, BROKEN OR SHOW ANY SIGNS OF TAMPERING.

Inactive ingredients

corn starch, lactose monohydrate, magnesium stearate, pregelatinized starch

Questions?

call 1-800-406-7984

Distributed by:
Ohm Laboratories Inc.
New Brunswick, NJ 08901

HOW SUPPLIED

Product: 50090-2387

NDC: 50090-2387-0 30 TABLET in a BLISTER PACK